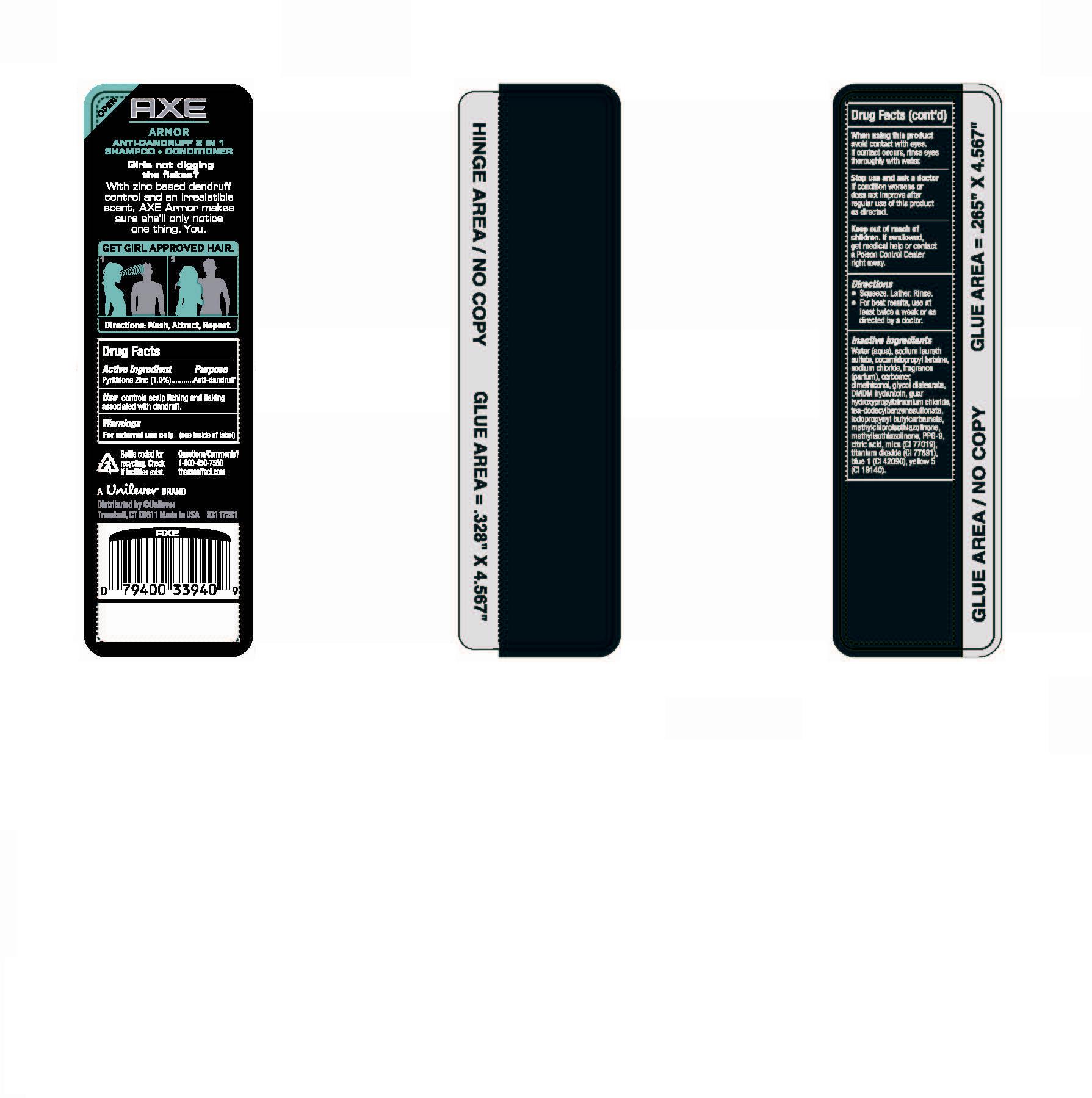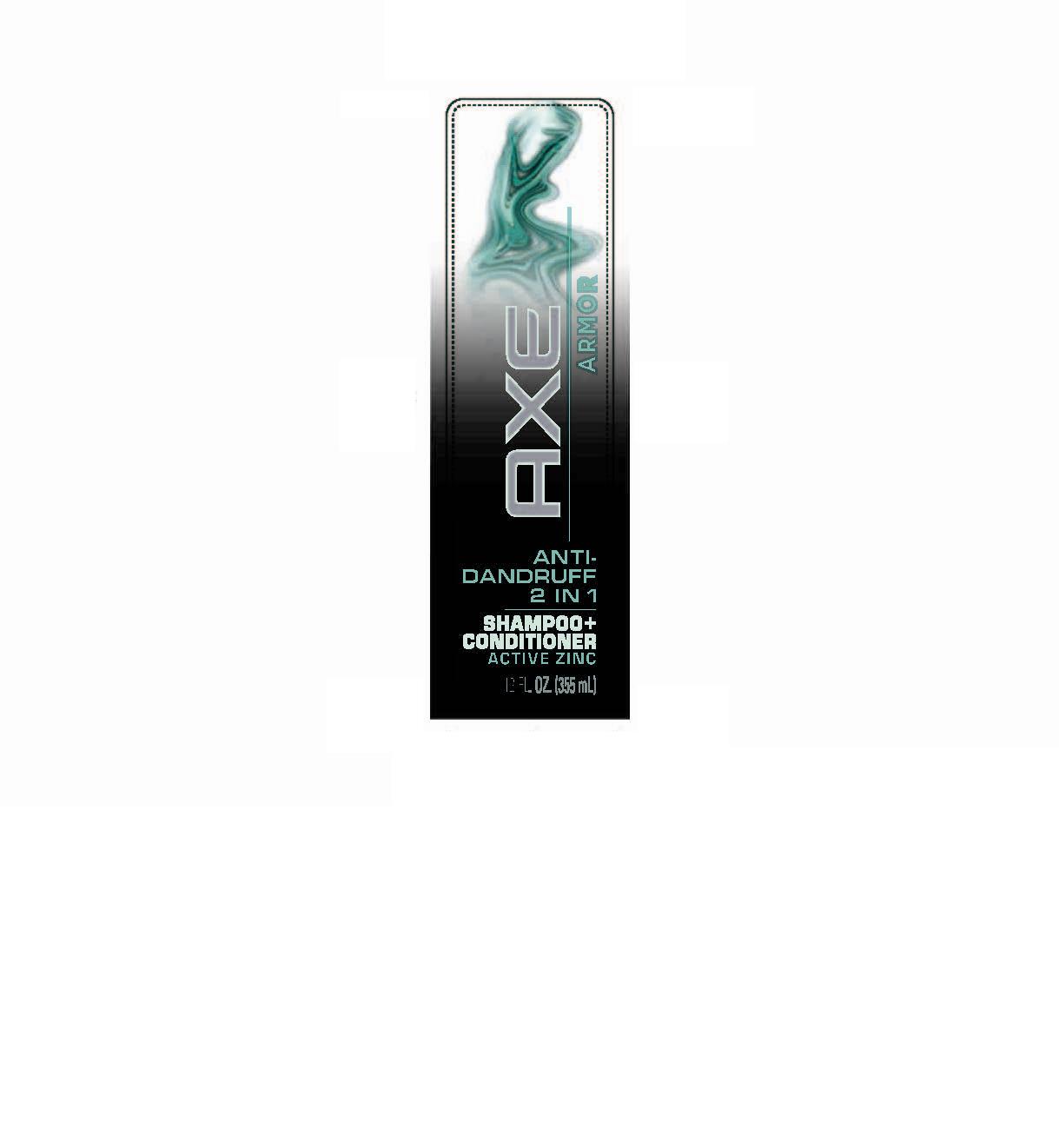 DRUG LABEL: Axe
NDC: 64942-1049 | Form: SHAMPOO
Manufacturer: Conopco Inc. d/b/a Unilever
Category: otc | Type: HUMAN OTC DRUG LABEL
Date: 20100303

ACTIVE INGREDIENTS: Pyrithione Zinc 1 mL/100 mL

Axe Freeze AntiDandruff shampoo+conditioner PDP front and back and drug facts box

Active Ingredient Purpose

Pyrithione Zinc (1.0%)....Anti-dandruff

PURPOSE

Use controls scalp itching and flaking associated with dandruff.

WARNINGS

For external use only (see inside of label)

When using this product avoid contact with eyes. If contact occurs, rinse eyes thoroughly with water.

Stop use and ask a doctor if condition worsens or does not improve after regular use of this product as directed.

Keep out of reach of children. If swallowed, get medical help or contact a Poison Control Center right away.

INACTIVE INGREDIENT

Water (Aqua), Sodium Laureth Sulfate, Cocamidopropyl Betaine, Sodium Chloride, Fragrance (Parfum), Carbomer, Dimethiconol, Glycol Distearate, DMDM Hydantoin, Guar Hydroxypropyltrimonium Chloride, TEA-Dodecylbenzenesulfonate, Iodopropynyl Butylcarbamate, Methylchloroisothiazolinone, Methylisothiazolinone, PPG-9, Citric Acid, Mica (CI 77019), Titanium Dioxide (CI 77891), Blue 1 (CI 42090), Yellow 5 (CI 19140).

Questions/Comments?

1-800-450-7580

theaxeeffect.com

PACKAGE LABEL

PDP 12 oz front

PACKAGE LABEL

PDP 12 oz back